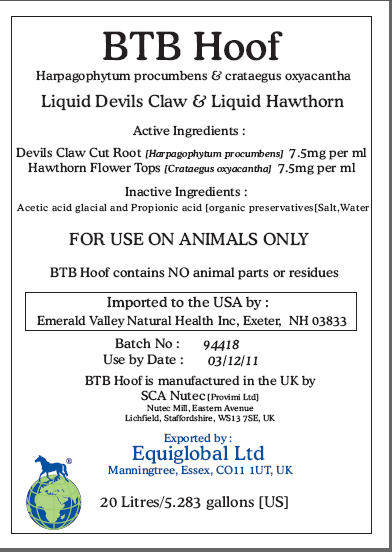 DRUG LABEL: BTB Hoof
NDC: 52338-389 | Form: EXTRACT
Manufacturer: SCA NuTec
Category: animal | Type: PRESCRIPTION ANIMAL DRUG LABEL
Date: 20100407

ACTIVE INGREDIENTS: HARPAGOPHYTUM PROCUMBENS ROOT 7.5 mg/1 mL; CRATAEGUS LAEVIGATA FLOWERING TOP 7.5 mg/1 mL

BTB Hoof

Harpagophytum procumbens and crataegus oxyacantha

Liquid Devils Claw and Liquid Hawthorn

Active Ingredients:

Devils Claw Cut Root [Harpagophytum procumbens] 7.5mg per ml
Hawthorn Flower Tops [Crataegus oxyacantha] 7.5mg per ml

Inactive Ingredients:

Acetic acid glacial and Propionic acid [organic preservatives[Salt,Water

WARNINGS

FOR USE ON ANIMALS ONLY

Imported to the USA by :
Emerald Valley Natural Health Inc, Exeter, NH 03833

Batch: 94418
Use by Date : 03/12/11
BTB Hoof is manufactured in the UK by
SCA Nutec [Provimi Ltd]
Nutec Mill, Eastern Avenue
Lichfield, Staffordshire, WS13 7SE, UK
Exported by :
Equiglobal Ltd
Manningtree, Essex, CO11 1UT, UK
20 Litres/5.283 gallons [US]